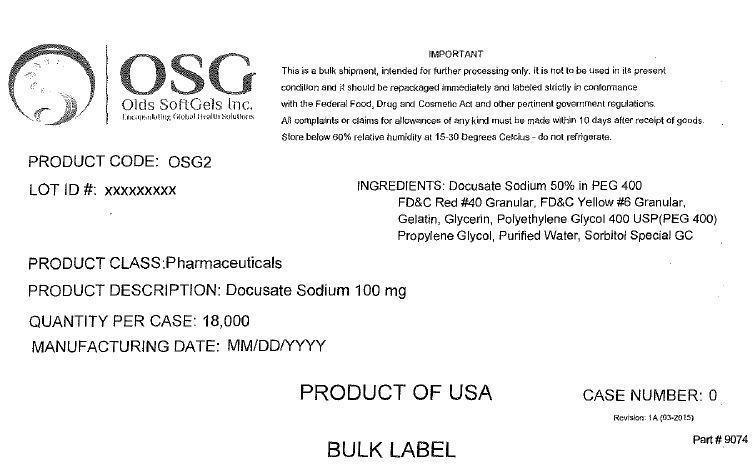 DRUG LABEL: Docusate Sodium
NDC: 69160-002 | Form: TABLET
Manufacturer: Olds Softgels Inc.
Category: otc | Type: HUMAN OTC DRUG LABEL
Date: 20200914

ACTIVE INGREDIENTS: DOCUSATE SODIUM 100 mg/1 1
INACTIVE INGREDIENTS: POLYETHYLENE GLYCOL 400; PROPYLENE GLYCOL; GELATIN; GLYCERIN; WATER; SORBITAN; SORBITOL; FD&C RED NO. 40; FD&C YELLOW NO. 6

ACTIVE INGREDIENT

Docusate Sodium 50%

PURPOSE

IMPORTANT

This is a bulk shipment, intended for further processing only. It is not to be used in its present condition and it should be repackaged immediately and labeled strictly in conformance with the Federal Food, Drug and Cosmetic Act and other pertinent government regulations.

Keep out of reach of children.

INDICATIONS AND USAGE

Olds SoftGels Inc

DOSAGE AND ADMINISTRATION

All complaints or claims for allowances of any kind must be made within 10 days after receipt of goods.

WARNINGS

All complaints or claims for allowances of any kind must be made within 10 days after receipt of goods.

INACTIVE INGREDIENT

INGREDIENTS: docusate sodium 50% in PEG 400 FD&C red #40 granular, FD&C yellow #6 granular, gelatin, glycerin, polyethylene glycol 400 USP (PEG 400) propylene glycol, purified water, sorbitol special GC